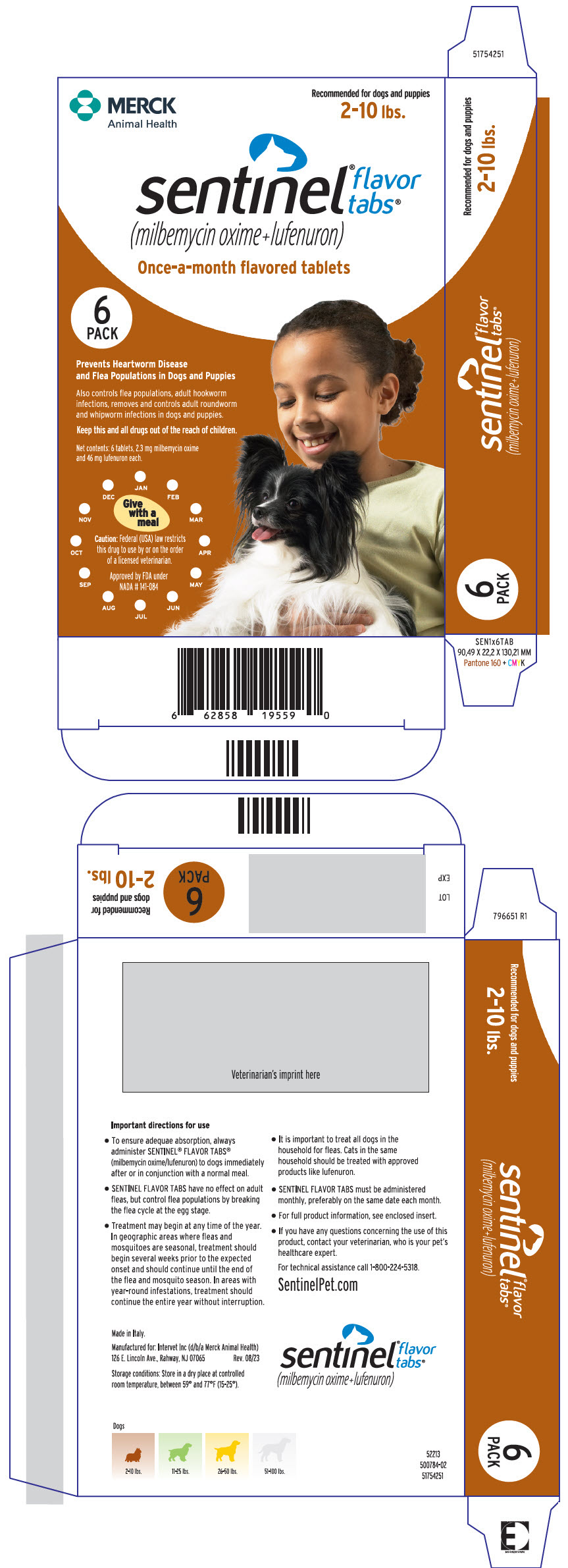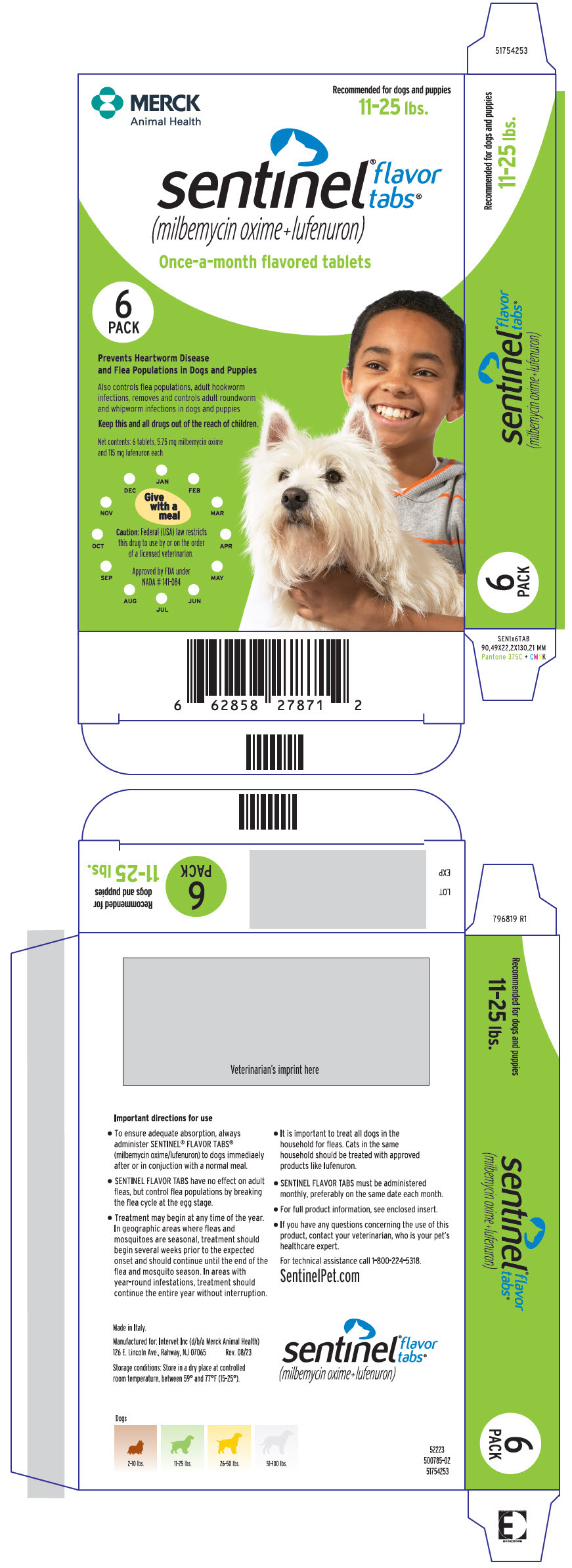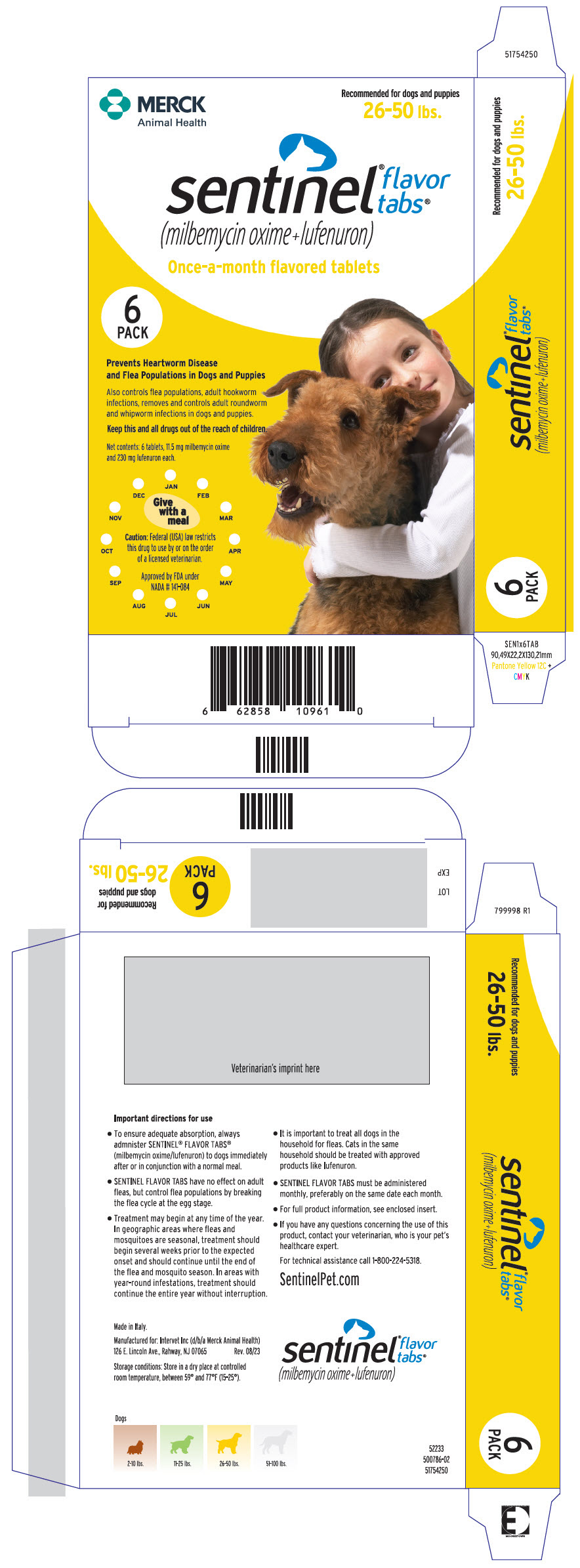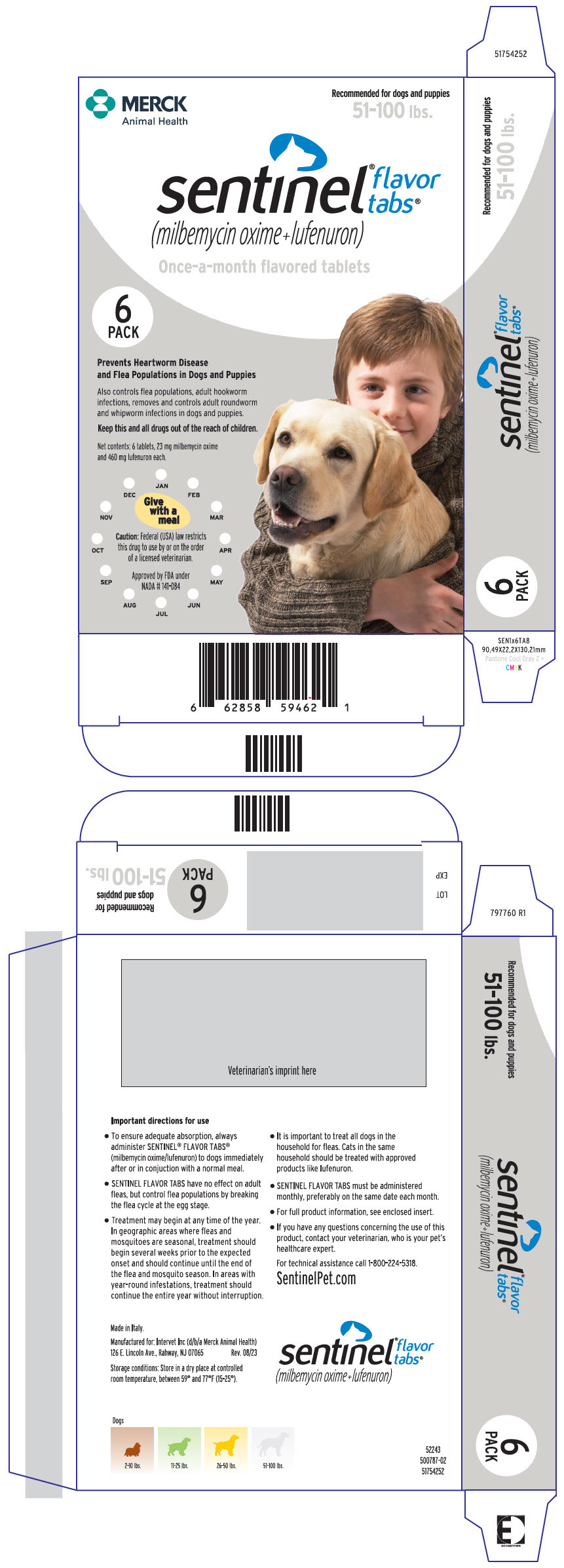 DRUG LABEL: Sentinel Flavor Tabs
NDC: 0061-5350 | Form: TABLET, CHEWABLE
Manufacturer: Merck Sharp & Dohme Corp.
Category: animal | Type: PRESCRIPTION ANIMAL DRUG LABEL
Date: 20241115

ACTIVE INGREDIENTS: MILBEMYCIN OXIME 2.3 mg/1 1; LUFENURON 46 mg/1 1

Sentinel® Flavor Tabs®
(milbemycin oxime+lufenuron)

The palatable once-a-month prescription tablet that prevents heartworm disease and flea populations in dogs and puppies. SENTINEL® FLAVOR TABS® (milbemycin oxime/lufenuron) also control flea populations and adult hookworms, and remove and control adult roundworm and whipworm infections in dogs and puppies.

Caution

Federal (USA) law restricts this drug to use by or on the order of a licensed veterinarian.

Warnings

Not for human use. Keep this and all drugs out of the reach of children.

Description

SENTINEL FLAVOR TABS are available in four tablet sizes in color-coded packages for oral administration to dogs and puppies according to their weight. (See Dosage Section). Each tablet is formulated to provide a minimum of 0.23 mg/pound (0.5 mg/kg) of milbemycin oxime and 4.55 mg/pound (10 mg/kg) body weight of lufenuron.

Milbemycin oxime consists of the oxime derivatives of 5-didehydromilbemycins in the ratio of approximately 80% A4 (C32H45NO7, MW 555.71) and 20% A3 (C31H43NO7, MW 541.68). Milbemycin oxime is classified as a macrocyclic anthelmintic.

Lufenuron is a benzoylphenylurea derivative with the following chemical composition:
N-[[[2,5-Dichloro-4-(1,1,2,3,3,3-hexafluoropropoxy)-phenyl]amino]carbonyl]-2,6-difluorobenzamide (C17H8Cl2F8N2O3, MW 511.15). Benzoylphenylurea compounds, including lufenuron, are classified as insect development inhibitors (IDIs).

Mode of Action

Milbemycin oxime, one active ingredient in SENTINEL FLAVOR TABS, is a macrocyclic anthelmintic which is believed to act by interfering with invertebrate neurotransmission. Milbemycin oxime eliminates the tissue stage of heartworm larvae and the adult stage of hookworm (Ancylostoma caninum), roundworm (Toxocara canis and Toxascaris leonina) and whipworm (Trichuris vulpis) infestations when administered orally according to the recommended dosage schedule.

Lufenuron, the other active ingredient in SENTINEL FLAVOR TABS, is an insect development inhibitor which breaks the flea life cycle by inhibiting egg development. Lufenuron's mode of action is interference with chitin synthesis, polymerization and deposition. Lufenuron has no effect on the adult flea. After biting a lufenuron-treated dog, the female flea ingests a blood meal containing lufenuron which is subsequently deposited in her eggs. Lufenuron prevents most flea eggs from hatching or maturing into adults and thus prevents and controls flea populations by breaking the life cycle. (See Efficacy).

Indications

SENTINEL FLAVOR TABS are indicated for use in dogs and puppies, four weeks of age and older, and two pounds body weight or greater. SENTINEL FLAVOR TABS are also indicated for the prevention of heartworm disease caused by Dirofilaria immitis, for the prevention and control of flea populations, the control of adult Ancylostoma caninum (hookworm), and the removal and control of adult Toxocara canis and Toxascaris leonina (roundworm) and Trichuris vulpis (whipworm) infections.

Lufenuron controls flea populations by preventing the development of flea eggs and does not kill adult fleas. Concurrent use of an adulticide product may be necessary for adequate control of adult fleas.

Without concurrent use of an adulticide, adequate flea control may not be achieved in dogs that have repeated exposure to flea infested animals or environments.

Precautions

Do not use in puppies less than four weeks of age and less than two pounds of body weight. Prior to administration of SENTINEL FLAVOR TABS, dogs should be tested for existing heartworm infections. Infected dogs should be treated to remove adult heartworms and microfilariae prior to initiating treatment with SENTINEL FLAVOR TABS. Mild, transient hypersensitivity reactions manifested as labored respiration, vomiting, salivation and lethargy have been noted in some treated dogs carrying a high number of circulating microfilariae. These reactions are presumably caused by release of protein from dead or dying microfilariae.

SENTINEL FLAVOR TABS immediately break the flea life cycle by inhibiting egg development. However, preexisting flea populations may continue to develop and emerge after treatment with SENTINEL FLAVOR TABS has begun. Based on results of clinical studies, this emergence generally occurs during the first 30-60 days.

Therefore, noticeable control may not be observed until several weeks after dosing when a preexisting infestation is present. Cooler geographic areas may have longer lag periods due to a prolonged flea life cycle. The concurrent use of an approved adulticide may be employed depending on the severity of the infestation.

If a SENTINEL FLAVOR TABS-treated dog comes in contact with a flea-infested environment, adult fleas may infest the treated animal. These adult fleas are unable to produce viable offspring. The temporary use of an adulticide product may be necessary to kill these adult fleas.

Efficacy: Milbemycin Oxime

Milbemycin oxime provided complete protection against heartworm infection in both controlled laboratory and clinical trials.

In laboratory studies, a single dose of milbemycin oxime at 0.5 mg/kg was effective in removing roundworms, hookworms and whipworms. In well-controlled clinical trials, milbemycin oxime was also effective in removing roundworms and whipworms and in controlling hookworms.

Efficacy: Lufenuron

Lufenuron provided 99% control of flea egg development for 32 days following a single dose of lufenuron at 10 mg/kg in studies using experimental flea infestations. In well-controlled clinical trials, when treatment with lufenuron tablets was initiated prior to the flea season, mean flea counts were lower on lufenuron-treated dogs versus placebo-treated dogs. After 6 monthly treatments, the mean number of fleas on lufenuron-treated dogs was approximately 4 compared to 230 on placebo-treated dogs.

When treatment was initiated during the flea season, lufenuron tablets were effective in controlling flea infestations on dogs that completed the study. The mean flea count per lufenuron-treated dog was approximately 74 prior to treatment but had decreased to 4 after six monthly doses of lufenuron. A topical adulticide was used in the first eight weeks of the study to kill the pre-existing adult fleas.

Safety: Milbemycin Oxime

Milbemycin oxime has been tested safely in over 75 different breeds of dogs, including collies, pregnant females, breeding males and females, and puppies over two weeks of age. In well-controlled clinical field studies 786 dogs completed treatment with milbemycin oxime. Milbemycin oxime was used safely in animals receiving frequently used veterinary products such as vaccines, anthelmintics, antibiotics, steroids, flea collars, shampoos and dips.

Two studies in heartworm-infected dogs were conducted which demonstrated mild, transient hypersensitivity reactions in treated dogs with high microfilaremia counts (see Precautions for reactions observed). Safety studies in pregnant dogs demonstrated that high doses (1.5 mg/kg = 3X) of milbemycin oxime given in an exaggerated dosing regimen (daily from mating through weaning), resulted in measurable concentrations of the drug in milk. Puppies nursing these females which received exaggerated dosing regimens demonstrated milbemycin-related effects. These effects were directly attributable to the exaggerated experimental dosing regimen. The product is normally intended for once-a-month administration only. Subsequent studies included using 3X daily from mating to one week before weaning and demonstrated no effects on the pregnant females or their litters. A second study where pregnant females were dosed once at 3X the monthly use rate either before, on the day of or shortly after whelping resulted in no effects on the puppies.

Some nursing puppies, at 2, 4, and 6 weeks of age, given greatly exaggerated oral doses of milbemycin oxime (9.6 mg/kg = 19X) exhibited signs typified by tremors, vocalization and ataxia. These effects were all transient and puppies returned to normal within 24 to 48 hours. No effects were observed in puppies given the recommended dose of milbemycin oxime (0.5 mg/kg). This product has not been tested in dogs less than 2.2 pounds in body weight.

A rising-dose safety study conducted in rough-coated collies manifested a clinical reaction consisting of ataxia, pyrexia and periodic recumbency in one of fourteen dogs treated with milbemycin oxime at 12.5 mg/kg (25X monthly use rate). Prior to receiving the 12.5 mg/kg dose (25X monthly use rate) on day 56 of the study, all animals had undergone an exaggerated dosing regimen consisting of 2.5 mg/kg milbemycin oxime (5X monthly use rate) on day 0, followed by 5.0 mg/kg (10X monthly use rate) on day 14 and 10.0 mg/kg (20X monthly use rate) on day 32. No adverse reactions were observed in any of the collies treated with this regimen up through the 10.0 mg/kg (20X monthly use rate) dose.

Safety: Lufenuron

Lufenuron tablets have been used and tested safely in over forty breeds of dogs, including pregnant females, breeding males and puppies over six weeks of age. In well-controlled clinical trials, 151 dogs completed treatment with lufenuron tablets. Lufenuron tablets were used safely in animals receiving frequently used veterinary products such as vaccines, anthelmintics, antibiotics and steroids. In a ten-month study, doses up to 10X the recommended dose rate of 10 mg/kg caused no overt toxicity. A single dose of 200 mg/kg (20X the recommended dose rate) had no marked effect on adult dogs, but caused decreased activity and appetite in eight week old puppies. Mean body weights of male and female puppies were higher in treated versus control group at the end of the study. In specifically designed target animal safety studies, lufenuron tablets were tested with concurrent administration of flea adulticides containing carbaryl, permethrin, chlorpyriphos and cythioate. No toxicity resulted from these combinations. Lufenuron tablets did not cause cholinesterase inhibition nor did they enhance cholinesterase inhibition caused by exposure to organophosphates.

Four reproductive safety studies were conducted in breeding dogs with lufenuron tablets: two laboratory and two well-controlled clinical studies. In one of the laboratory studies, where lufenuron was administered to beagle dogs at doses equivalent to 90X (3X daily) the monthly recommended dose of 10 mg/kg, the ratio of gravid females to females mated was 8/8 or 100% in the control group and 6/9 or 67% in the lufenuron-treated group. The mean number of pups per litter was two animals higher in the treated versus control groups and the mean birth weights of pups from treated females in this study was lower than control groups.

These pups grew at a similar rate to control pups. There was a higher incidence of four clinical signs in the lufenuron-treated versus control group: nasal discharge, pulmonary congestion, diarrhea/dehydration and sluggishness. The incidence of these signs was transient and decreasing by the end of lactation. Results from three additional reproductive safety studies, one laboratory and two clinical field studies evaluating eleven breeds of dogs, did not demonstrate any adverse findings for the reproductive parameters measured including fertility, pup birth weights and pup clinical signs after administration of lufenuron up to 5X the recommended monthly use rate.

Data from analysis of milk from lactating animals treated with lufenuron tablets at 2X and 6X the recommended monthly use rate demonstrates that lufenuron concentrates in the milk of these dogs. The average milk:blood concentration ratio was approximately 60 (i.e., 60X higher drug concentrations in the milk compared to drug levels in the blood of treated females). Nursing puppies averaged 8-9 times higher blood concentrations of lufenuron compared to their dams.

Dosage

SENTINEL FLAVOR TABS are given orally, once a month, at the recommended minimum dosage of 0.23 mg/lb (0.5 mg/kg) milbemycin oxime and 4.55 mg/lb (10mg/kg) lufenuron. Dogs over 100 lbs are provided the appropriate combination of tablets.

Administration

TO ENSURE ADEQUATE ABSORPTION, ALWAYS ADMINISTER SENTINEL FLAVOR TABS TO DOGS IMMEDIATELY AFTER OR IN CONJUNCTION WITH A NORMAL MEAL.

SENTINEL FLAVOR TABS are palatable and most dogs will consume the tablet when offered by the owner. As an alternative to direct dosing, the tablets can be hidden in food. Be certain the dog consumes the entire tablet or tablets.

Administer SENTINEL FLAVOR TABS to dogs immediately after or in conjunction with a normal meal. Food is essential for adequate absorption of lufenuron. Watch the dog closely following administration to be sure the entire dose has been consumed. If it is not entirely consumed, redose with the full recommended dose as soon as possible.

Recommended Dosage Schedule
Body Weight | Milbemycin Oxime Per Tablet | Lufenuron Per Tablet
2 to 10 lbs. | 2.3 mg | 46 mg
11 to 25 lbs. | 5.75 mg | 115 mg
26 to 50 lbs. | 11.5 mg | 230 mg
51 to 100 lbs. | 23 mg | 460 mg

SENTINEL FLAVOR TABS must be administered monthly, preferably on the same date each month. Treatment with SENTINEL FLAVOR TABS may begin at any time of year. In geographic areas where mosquitoes and fleas are seasonal, the treatment schedule should begin one month prior to the expected onset and should continue until the end of "mosquito and flea season." In areas with year-round infestations, treatment should continue through the entire year without interruption.

If a dose is missed and a 30-day interval between dosing is exceeded, administer SENTINEL FLAVOR TABS immediately and resume the monthly dosing schedule. If SENTINEL FLAVOR TABS replace daily diethylcarbamazine (DEC) for heartworm prevention, the first dose must be given within 30 days after the last dose of DEC.

Adverse Reactions

The following adverse reactions have been reported in dogs after giving milbemycin oxime or lufenuron: vomiting, depression/lethargy, pruritus, urticaria, diarrhea, anorexia, skin congestion, ataxia, convulsions, hypersalivation, and weakness.

To report suspected adverse drug events, contact Merck Animal Health at 1-800-224-5318. For additional information about adverse drug experience reporting for animal drugs, contact FDA at 1-888-FDA-VETS or www.fda.gov/reportanimalae.

How Supplied

SENTINEL FLAVOR TABS are available in four tablet sizes (see Dosage section) formulated according to the weight of the dog. Each tablet size is available in color-coded packages of 6 or 12 tablets each, which are packaged 10 per display carton.

Storage Conditions

Store in a dry place at controlled room temperature, between 59° and 77°F (15-25°C).

Questions? Comments?
Please Call 1-800-224-5318
Visit our website at SentinelPet.com

Manufactured for:
Intervet Inc (d/b/a Merck Animal Health)
126 E. Lincoln Ave.
Rahway, NJ 07065
Approved by FDA under NADA # 141-084
© 2023 Merck & Co., Inc., Rahway, NJ, USA and its affiliates. All rights reserved.

Rev. 08/23

MERCK
Animal Health

799679 R1

302238-02 - 51754254

PRINCIPAL DISPLAY PANEL - 2.3 mg/46 mg Blister Pack Carton

MERCK
Animal Health

Recommended for dogs and puppies
2-10 lbs.

sentinel®
flavor
tabs®
(milbemycin oxime+lufenuron)

Once-a-month flavored tablets

6
PACK

Prevents Heartworm Disease
and Flea Populations in Dogs and Puppies

Also controls flea populations, adult hookworm
infections, removes and controls adult roundworm
and whipworm infections in dogs and puppies.

Keep this and all drugs out of the reach of children.

Net contents: 6 tablets, 2.3 mg milbemycin oxime
and 46 mg lufenuron each.

JAN
FEB
MAR
APR
MAY
JUN
JUL
AUG
SEP
OCT
NOV
DEC

Give
with a
meal

Caution: Federal (USA) law restricts
this drug to use by or on the order
of a licensed veterinarian.

Approved by FDA under
NADA # 141-084

PRINCIPAL DISPLAY PANEL - 5.75 mg/115 mg Blister Pack Carton

MERCK
Animal Health

Recommended for dogs and puppies
11-25 lbs.

sentinel®
flavor
tabs®
(milbemycin oxime+lufenuron)

Once-a-month flavored tablets

6
PACK

Prevents Heartworm Disease
and Flea Populations in Dogs and Puppies

Also controls flea populations, adult hookworm
infections, removes and controls adult roundworm
and whipworm infections in dogs and puppies

Keep this and all drugs out of the reach of children.

Net contents: 6 tablets, 5.75 mg milbemycin oxime
and 115 mg lufenuron each.

JAN
FEB
MAR
APR
MAY
JUN
JUL
AUG
SEP
OCT
NOV
DEC

Give
with a
meal

Caution: Federal (USA) law restricts
this drug to use by or on the order
of a licensed veterinarian.

Approved by FDA under
NADA # 141-084

PRINCIPAL DISPLAY PANEL - 11.5 mg/230 mg Blister Pack Carton

MERCK
Animal Health

Recommended for dogs and puppies
26-50 lbs.

sentinel®
flavor
tabs®
(milbemycin oxime+lufenuron)

Once-a-month flavored tablets

6
PACK

Prevents Heartworm Disease
and Flea Populations in Dogs and Puppies

Also controls flea populations, adult hookworm
infections, removes and controls adult roundworm
and whipworm infections in dogs and puppies.

Keep this and all drugs out of the reach of children.

Net contents: 6 tablets, 11.5 mg milbemycin oxime
and 230 mg lufenuron each.

JAN
FEB
MAR
APR
MAY
JUN
JUL
AUG
SEP
OCT
NOV
DEC

Give
with a
meal

Caution: Federal (USA) law restricts
this drug to use by or on the order
of a licensed veterinarian.

Approved by FDA under
NADA # 141-084

PRINCIPAL DISPLAY PANEL - 23 mg/460 mg Blister Pack Carton

MERCK
Animal Health

Recommended for dogs and puppies
51-100 lbs.

sentinel®
flavor
tabs®
(milbemycin oxime+lufenuron)

Once-a-month flavored tablets

6
PACK

Prevents Heartworm Disease
and Flea Populations in Dogs and Puppies

Also controls flea populations, adult hookworm
infections, removes and controls adult roundworm
and whipworm infections in dogs and puppies.

Keep this and all drugs out of the reach of children.

Net contents: 6 tablets, 23 mg milbemycin oxime
and 460 mg lufenuron each.

JAN
FEB
MAR
APR
MAY
JUN
JUL
AUG
SEP
OCT
NOV
DEC

Give
with a
meal

Caution: Federal (USA) law restricts
this drug to use by or on the order
of a licensed veterinarian.

Approved by FDA under
NADA # 141-084